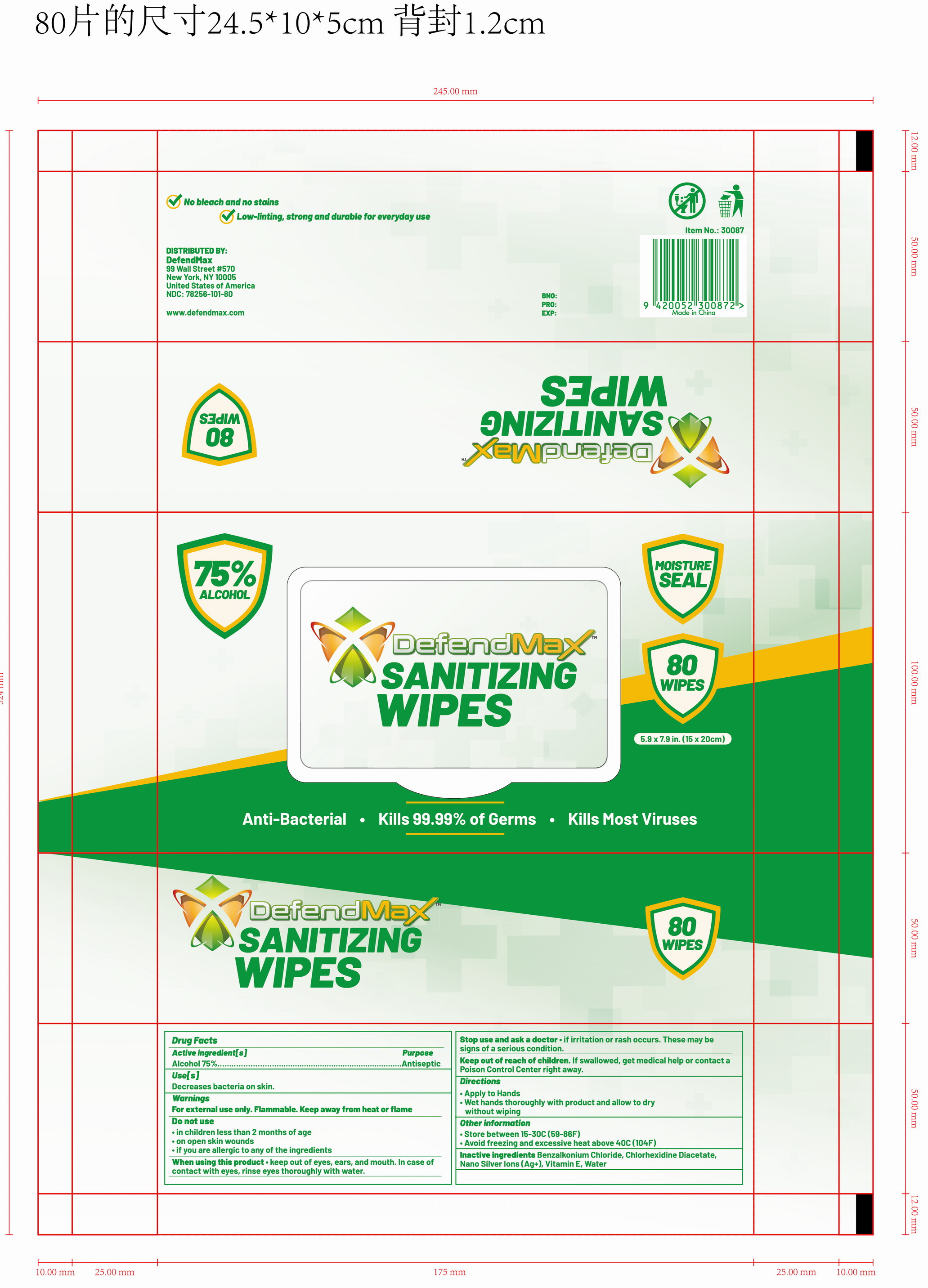 DRUG LABEL: Sanitizing Wipes
NDC: 78183-002 | Form: CLOTH
Manufacturer: Kunming Ansheng Industry & Trade Co., Ltd.
Category: otc | Type: HUMAN OTC DRUG LABEL
Date: 20200702

ACTIVE INGREDIENTS: ALCOHOL 0.75 U/1 U
INACTIVE INGREDIENTS: SILVER ACETATE 0.00004 U/1 U; CHLORHEXIDINE ACETATE 0.001 U/1 U; BENZALKONIUM CHLORIDE 0.001 U/1 U; WATER

Defendmax Sanitizing Wipes

Active Ingredient(s)

Alcohol 75% v/v;

Chlorohexidine Diacetate 0.1% v/v;

Benzalkonium 0.1% v/v;

Purpose

Antibacterial

Use

For hand sanitizing to decrease bacterial on the skin.

Warnings

For external use only. Flammable. Keep away from heat or flame

Do not use

- on infants less than 2 months of age
- on open skin wounds

When using this product keep out of eyes, ears, and mouth. In case of contact with eyes, rinse eyes thoroughly with water.

Stop use and ask a doctor if irritation or rash occurs. These may be signs of a serious condition.

Keep out of reach of children. If swallowed, get medical help or contact a Poison Control Center right away.

Directions

1, Open sticker, pull out the wipe and close sticker tightly.

2, Dispose of used wipes in trash, DO NOT FLUSH.

Other information

- Store between 15-30℃ (59-86F)
- Avoid freezing and excessive heat about 40℃ (104F)

Inactive ingredients

Inactive ingredients: Water, Chlorohexidine Diacetate, Benzalkonium Chloride, Nano Silver Ion (Ag+)

Package Label - Principal Display Panel

80 wipes in 1 bag. NDC: 78183-002-01;